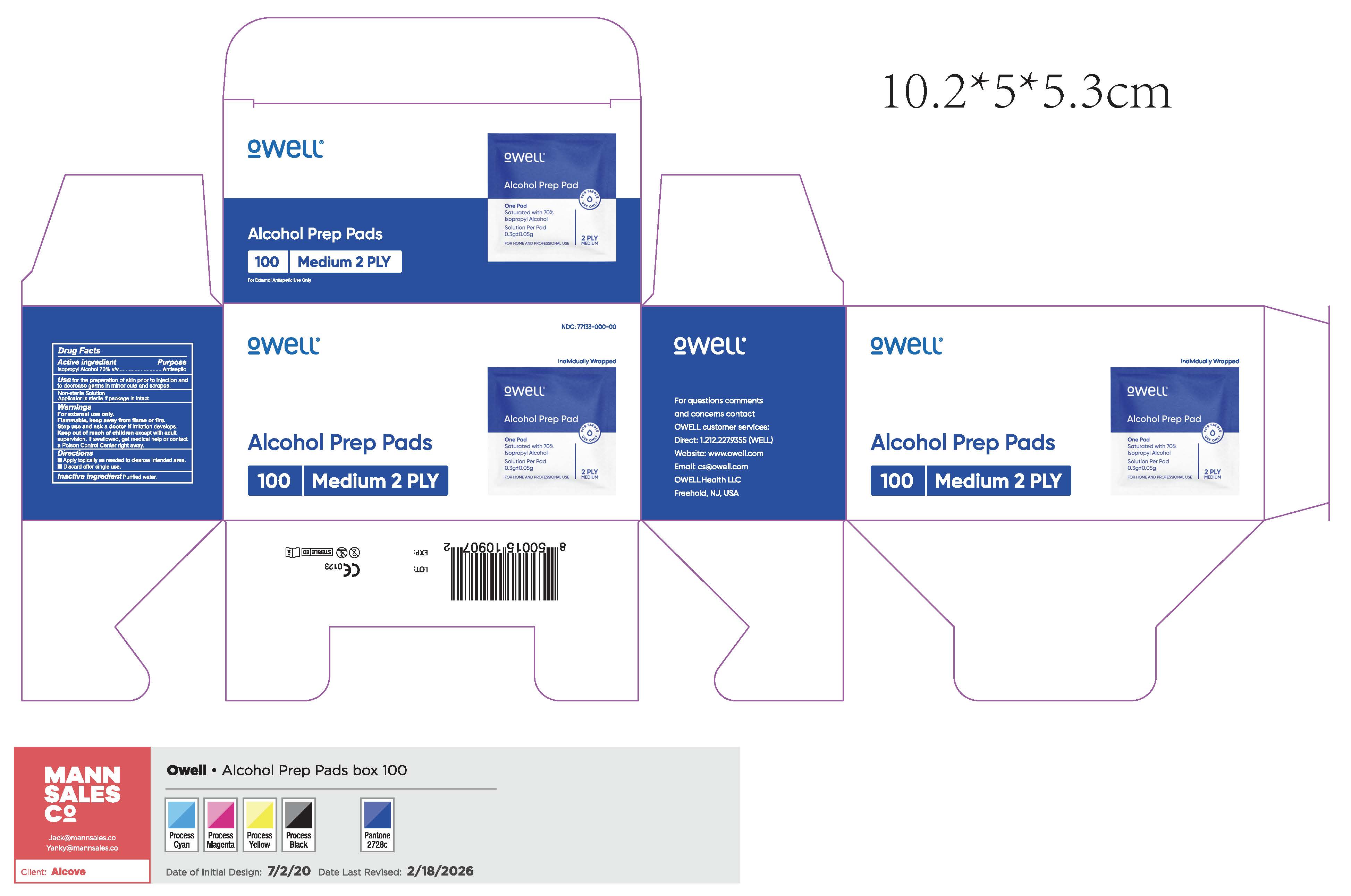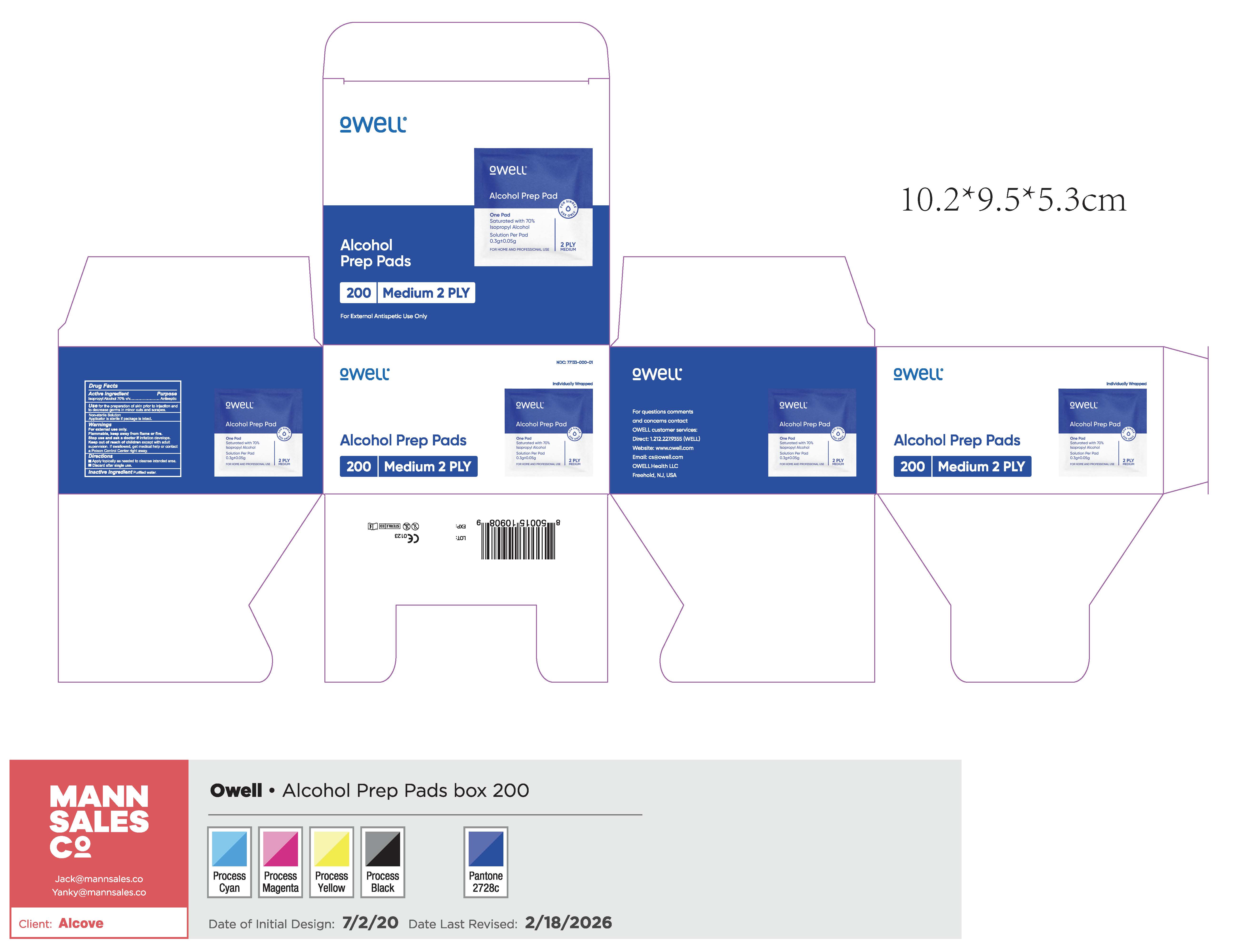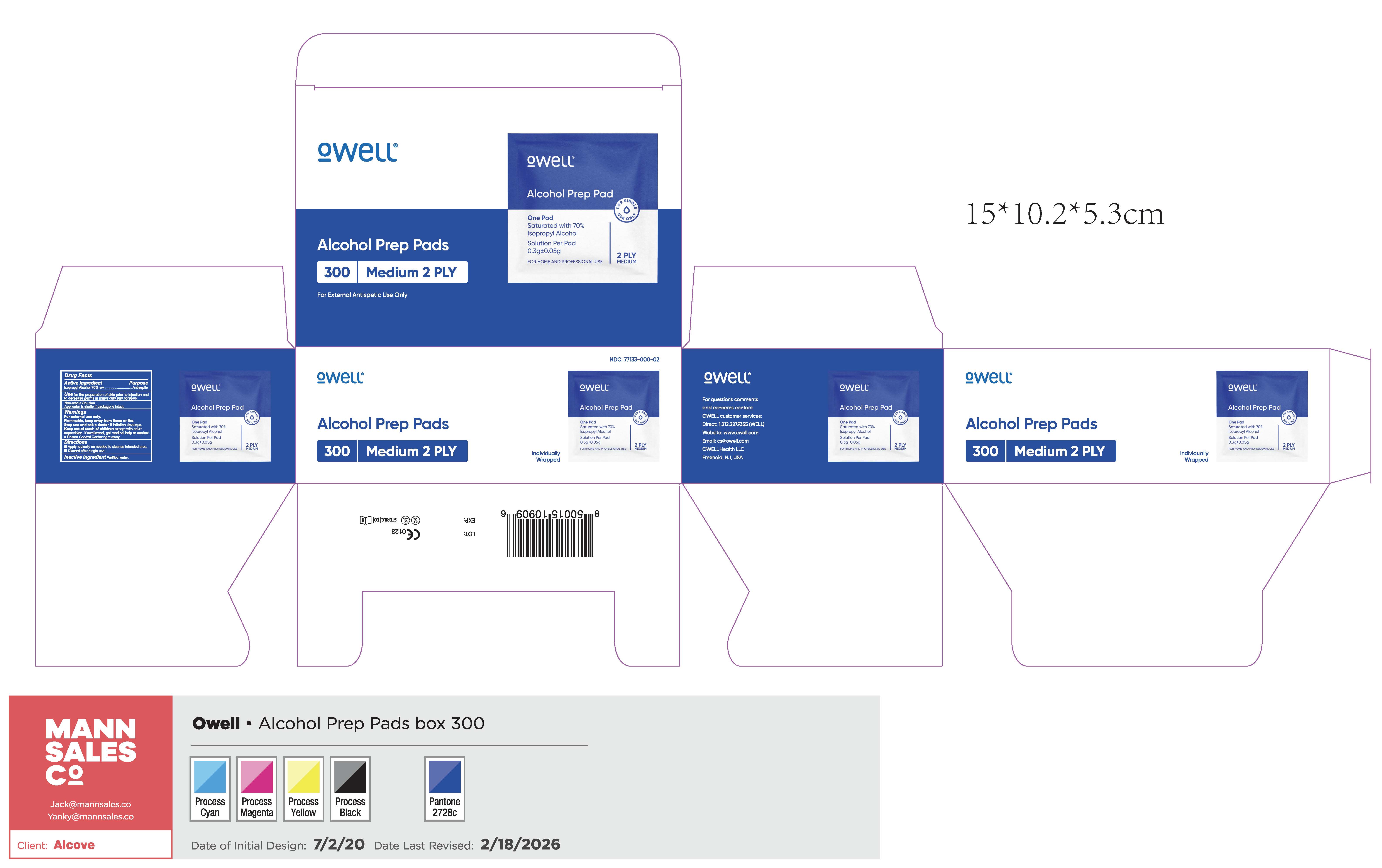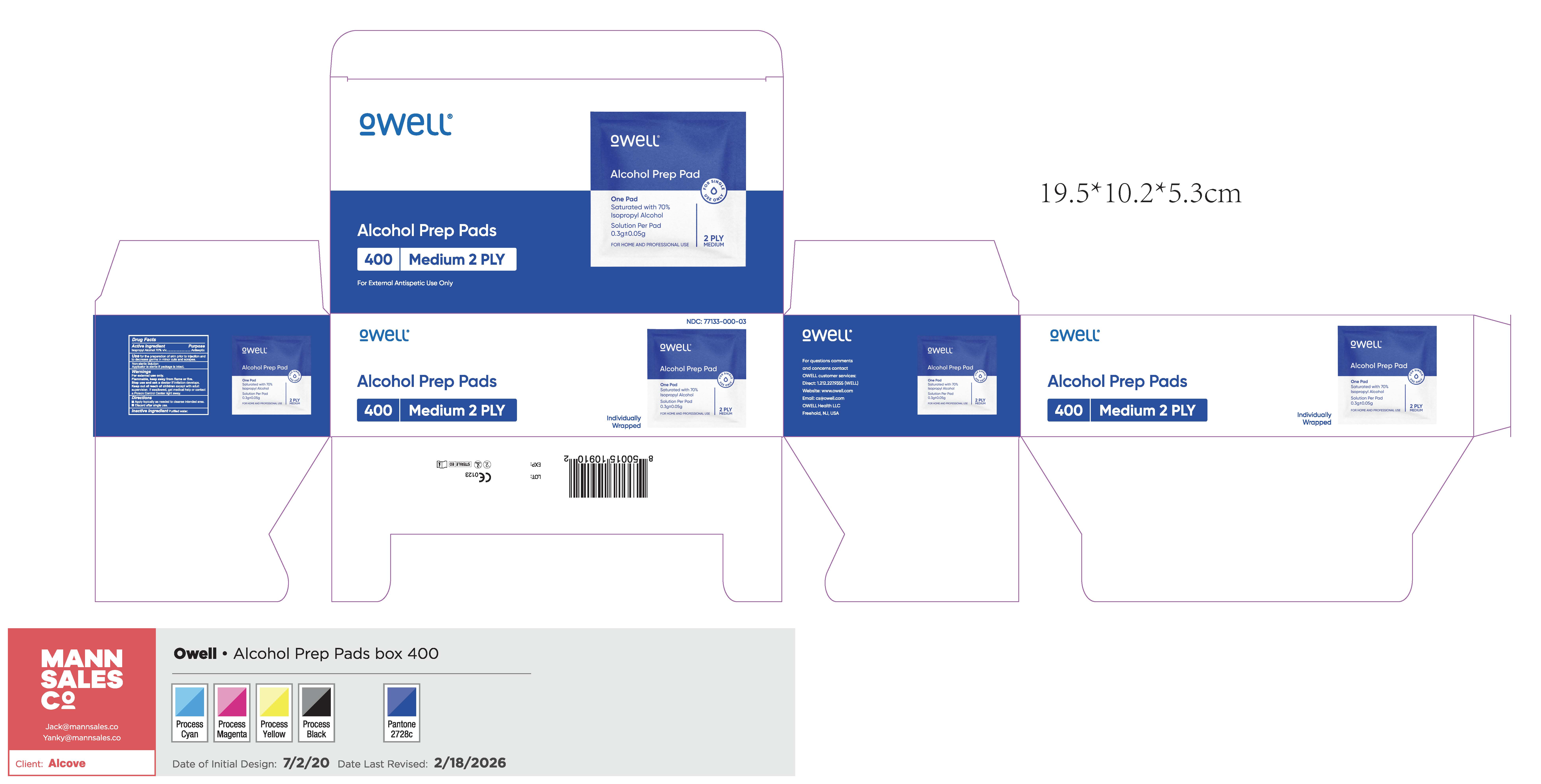 DRUG LABEL: Alcohol Prep Pads
NDC: 77133-003 | Form: CLOTH
Manufacturer: ALCOVE BRANDS
Category: otc | Type: HUMAN OTC DRUG LABEL
Date: 20260224

ACTIVE INGREDIENTS: ISOPROPYL ALCOHOL 0.7 mL/1 mL
INACTIVE INGREDIENTS: WATER

Alcohol Prep Pads

Active ingredient

Isopropyl Alcohol 70% v/v

Purpose

Antiseptic

Use

for the preparation of skin prior to injection and to decrease germs in minor cuts and scrapes.

Non-sterile Solution

Applicator is sterile if package is intact.

Warnings

For external use only.

Flammable, keep away from flame or fire.

Stop use and ask a doctor if

irritation develops.

Keep out of reach of children

except with adult supervision. If swallowed, get medical help or contact a Poison Control Cenre right away.

Directions

- Apply topically as needed to cleanse intended area.
- Discard after single use.

Inactive ingredient

Purified water.

Package Labeling:77133-003-00

77133-003-00

Package Labeling:77133-003-01

77133-003-01

Package Labeling:77133-003-02

77133-003-02

Package Labeling:77133-003-03

77133-003-03